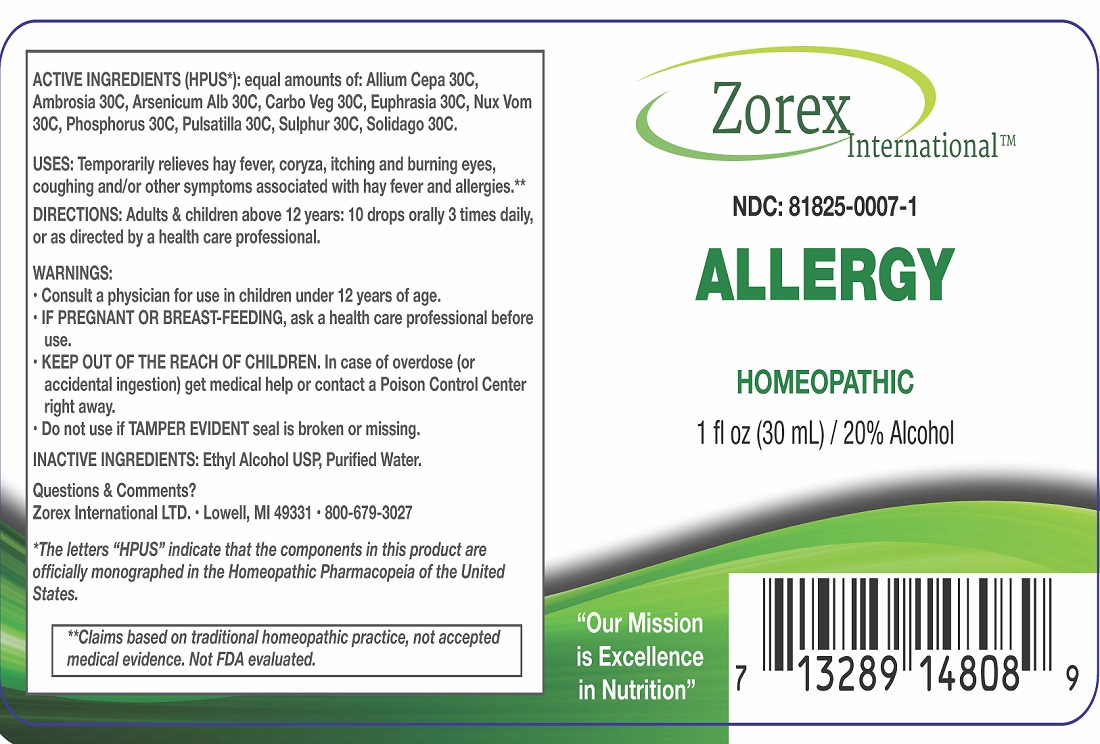 DRUG LABEL: Allergy
NDC: 81825-0007 | Form: LIQUID
Manufacturer: Zorex International
Category: homeopathic | Type: HUMAN OTC DRUG LABEL
Date: 20181221

ACTIVE INGREDIENTS: ONION 30 [hp_C]/1 mL; AMBROSIA ARTEMISIIFOLIA WHOLE 30 [hp_C]/1 mL; ACTIVATED CHARCOAL 30 [hp_C]/1 mL; EUPHRASIA STRICTA 30 [hp_C]/1 mL; STRYCHNOS NUX-VOMICA SEED 30 [hp_C]/1 mL; PHOSPHORUS 30 [hp_C]/1 mL; PULSATILLA VULGARIS WHOLE 30 [hp_C]/1 mL; SULFUR 30 [hp_C]/1 mL; SOLIDAGO VIRGAUREA FLOWERING TOP 30 [hp_C]/1 mL
INACTIVE INGREDIENTS: ALCOHOL; WATER

Allergy

ACTIVE INGREDIENT

ACTIVE INGREDIENTS (*HPUS): equal amounts of: Allium Cepa 30C, Ambrosia 30C, Arsenicum Alb 30C, Carbo Veg 30C, Euphrasia 30C, Nux Vom 30C, Phosphorus 30C, Pulsatilla 30C, Sulphur 30C, Solidago 30C

INDICATIONS AND USAGE

USES: Temporarily relieves hay fever, coryza, itching and burning eyes, coughing and/or other symptoms associated with hay fever and allergies.**

PURPOSE

USES: Temporarily relieves hay fever, coryza, itching and burning eyes, coughing and/or other symptoms associated with hay fever and allergies.**

DOSAGE AND ADMINISTRATION

DIRECTIONS: Adults & children above 12 years: 10 drops orally 3 times daily, or as directed by a health care professional.

KEEP OUT OF REACH OF CHILDREN

KEEP OUT OF THE REACH OF CHILDREN. In case of overdose (or accidental ingestion) get medical help or contact a Poison Control Center right away.

WARNINGS:

- Consult a physician for use in children under 12 years of age.
- IF PREGNANT OR BREAST-FEEDING, ask a health care professional before use.
- KEEP OUT OF THE REACH OF CHILDREN. In case of overdose (or accidental ingestion) get medical help or contact a Poison Control Center right away.
- Do not use if TAMPER EVIDENT seal is broken or missing.

INACTIVE INGREDIENTS: Ethyl Alcohol USP, Purified Water

QUESTIONS & COMMENTS?

Zorex International LTD. / Lowell, MI 49331 / 800-679-3027

REFERENCES

*The letters "HPUS" indicate the components in the product are officially monographed in the Homeopathic Pharmacopeia of the United States.

**Claims based on traditional homeopathic practice, not accepted medical evidence. Not FDA evaluated.

PACKAGE LABEL

NDC:81825-0007-1

Allergy

HOMEOPATHIC

1 fl oz (30mL) / 20% Alcohol